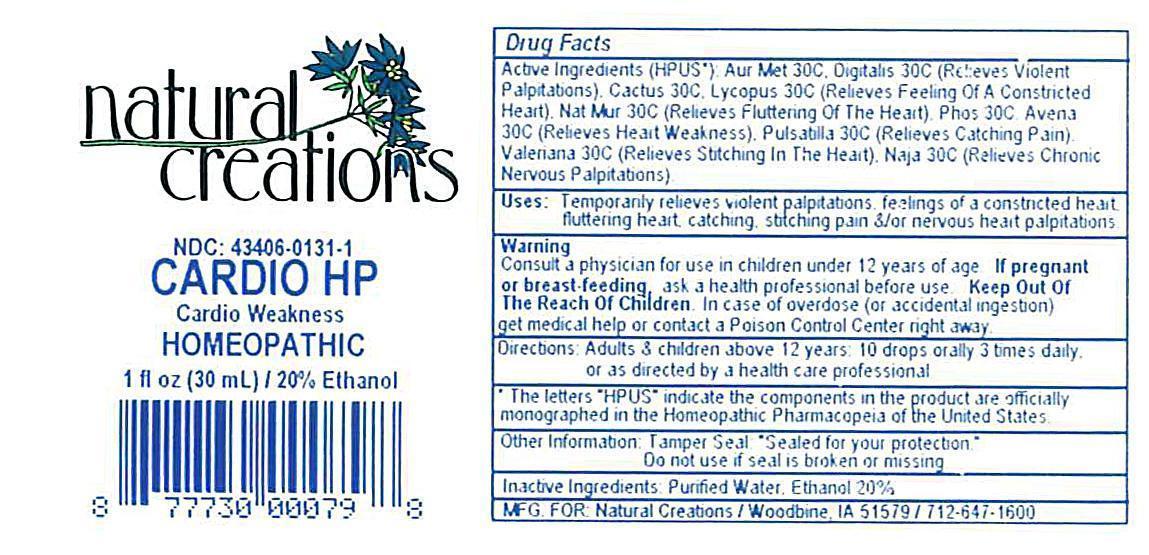 DRUG LABEL: Cardio HP
NDC: 43406-0131 | Form: LIQUID
Manufacturer: Natural Creations, Inc.
Category: homeopathic | Type: HUMAN OTC DRUG LABEL
Date: 20121010

ACTIVE INGREDIENTS: GOLD 30 [hp_C]/1 mL; SELENICEREUS GRANDIFLORUS STEM 30 [hp_C]/1 mL; AVENA SATIVA FLOWERING TOP 30 [hp_C]/1 mL; DIGITALIS PURPUREA WHOLE 30 [hp_C]/1 mL; LYCOPUS VIRGINICUS 30 [hp_C]/1 mL; NAJA NAJA VENOM 30 [hp_C]/1 mL; SODIUM CHLORIDE 30 [hp_C]/1 mL; PHOSPHORUS 30 [hp_C]/1 mL; PULSATILLA PATENS 30 [hp_C]/1 mL; VALERIAN 30 [hp_C]/1 mL
INACTIVE INGREDIENTS: WATER; ALCOHOL

CARDIO HP

ACTIVE INGREDIENT

ACTIVE INGREDIENTS (HPUS*): Aurum Metallicum 30C, Avena Sativa 30C, Cactus Grandiflorus 30C, Digitalis Purpurea 30C, Lycopus Virginicus 30C, Naja Tripudains 30C, Natrum Muriaticum 30C, Phosphorus 30C, Pulsatilla Nigricans 30C, Valeriana Officinalis 30C

INDICATIONS AND USAGE

USES: Temporarily relievs violent palpitations, feelings of a constricted heart, fluttering heart, catching, stitching pain, &/or nervous heart palpitations.

WARNING:

Consult a physician for use in children under 12 years of age. IF PREGNANT OR BREAST-FEEDING, ask a health care professional before use. KEEP OUT OF THE REACH OF CHILDREN. In case of overdose (or accidental ingestion) get medical help or contact a Poison Control Center right away.

DOSAGE AND ADMINISTRATION

DIRECTIONS: Adults and children above 12 years: 10 drops orally 3 times daily, or as directed by a health care professional.

OTHER INFORMATION: Tamper Seal: "Sealed for your protection."

Do not use if seal is broken or missing.

REFERENCES

*The letters "HPUS" indicate the components in the product are officially monographed in the Homeopathic Pharmacopeia of the United States.

INACTIVE INGREDIENTS: Purified Water, USP Ethanol Alcohol 20%

QUESTIONS AND COMMENTS?

MFG FOR: Natural Creations / Woodbine, IA / 51579 712.647.1600

LOT:

PURPOSE

USES: Temporarily relieves violent palpitations, feelings of a constricted heart, fluttering heart, catching, stitching pain, &/or nervous heart palpitations.

KEEP OUT OF REACH OF CHILDREN

KEEP OUT OF THE REACH OF CHILDREN. In case of overdose (or accidental ingestion) get medical help or contact a Poison Control Center.

PACKAGE LABEL

NDC: 43406-0131-1

CARDIO HP

Cardio Weakness

HOMEOPATHIC

1 fl oz (30 mL) / 20% Ethanol

UPC: 877730000798